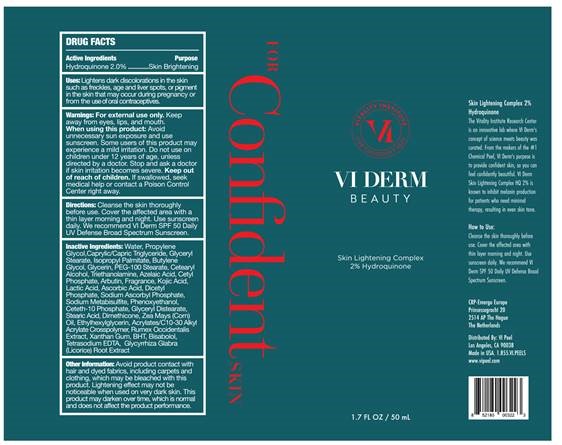 DRUG LABEL: HQ Plus Brightening Cream
NDC: 70484-004 | Form: CREAM
Manufacturer: Vi Medical Products Inc.
Category: otc | Type: HUMAN OTC DRUG LABEL
Date: 20200214

ACTIVE INGREDIENTS: HYDROQUINONE 1 g/50 mL
INACTIVE INGREDIENTS: WATER; PROPYLENE GLYCOL; MEDIUM-CHAIN TRIGLYCERIDES; GLYCERYL MONOSTEARATE; ISOPROPYL PALMITATE; BUTYLENE GLYCOL; GLYCERIN; PEG-100 STEARATE; CETOSTEARYL ALCOHOL; AZELAIC ACID; CETYL PHOSPHATE; TROLAMINE; ARBUTIN; KOJIC ACID; ASCORBIC ACID; DIHEXADECYL PHOSPHATE; CETETH-10 PHOSPHATE; SODIUM ASCORBYL PHOSPHATE; DIMETHICONE; LEVOMENOL; GLYCYRRHIZA GLABRA; SODIUM METABISULFITE; CORN OIL; BUTYLATED HYDROXYTOLUENE; LACTIC ACID; XANTHAN GUM; CARBOMER INTERPOLYMER TYPE A (ALLYL SUCROSE CROSSLINKED); EDETATE SODIUM; ETHYLHEXYLGLYCERIN; PHENOXYETHANOL

VI Derm HQ Plus - Brightening Cream

Active Ingredient Purpose

Hydroquinone 2.0% Skin Brightening

Use

- Skin brightening formula that may help reduce discolorations

Keep out of reach of children. If swallowed seek medical help or contact a Poison Control Center right away.

INDICATIONS AND USAGE

Stop and ask a doctor if skin irritation becomes severe

Warning

- For External Use only. When using this product: avoid unnecessary sun exposure and use a suncreen
- Some Users of this product may experience a mild irritation
- Do not use on children under 12 years of age, unless directed by a doctor

Directions

- Cleanse the skin thoroughly before use. Cover the affected area with thin layer morning and night. Use Sunscreen daily. We recommend VI Derm SPF50+

INACTIVE INGREDIENT

Water (Aqua), Propylene Glycol, Caprylic/Capric Triglyceride, Glyceryl Stearate, Isopropyl Palmitate, Butylene Glycol, Glycerin, PEG-100 Stearate, Cetearyl Alcohol, Azelaic Acid, Cetyl Phosphate, Triethanolamine, Arbutin, Fragrance, Kojic Acid, Rumex Occidentalis Extract, Ascorbic Acid, Dicetyl Phosphate, Ceteth-10 Phosphate, Sodium Ascorbyl Phosphate, Dimethicone, Bisabolol, Glycyrrhiza Glabra (Licorice) Root Extract, Sodium Metabisulfite, Zea Mays (Corn) Oil, BHT, Lactic Acid, Xanthan Gum, Acrylates/C10-30 Alkyl Acrylate Crosspolymer, Tetrasodium EDTA, Ethylhexylglycerin, Phenoxyethanol

PACKAGE LABEL

VI Derm HQ Plus

Brightening Cream

1.75 FL OZ/50 mL